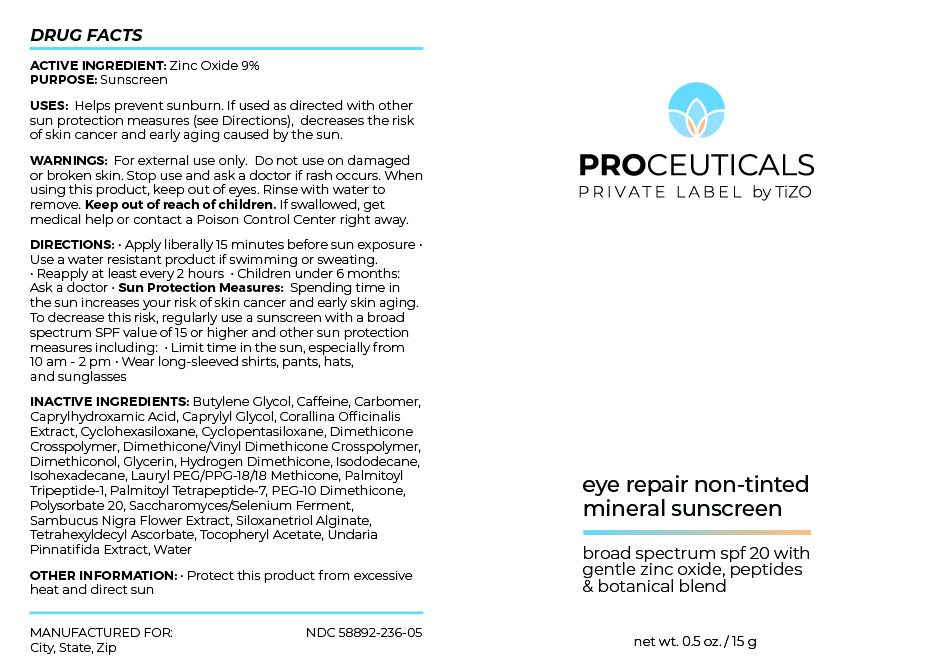 DRUG LABEL: PROCEUTICALS PRIVATE LABEL by TiZO eye repair non-tinted mineral sunscreen
NDC: 58892-236 | Form: CREAM
Manufacturer: Fallien Cosmeceuticals, LTD
Category: otc | Type: HUMAN OTC DRUG LABEL
Date: 20240927

ACTIVE INGREDIENTS: ZINC OXIDE 90 mg/1 g
INACTIVE INGREDIENTS: TETRAHEXYLDECYL ASCORBATE; .ALPHA.-TOCOPHEROL ACETATE; CAPRYLHYDROXAMIC ACID; CORALLINA OFFICINALIS; POLYSORBATE 20; DIMETHICONE CROSSPOLYMER (450000 MPA.S AT 12% IN CYCLOPENTASILOXANE); DIMETHICONE/VINYL DIMETHICONE CROSSPOLYMER (SOFT PARTICLE); HYDROGEN DIMETHICONE (20 CST); CYCLOMETHICONE 6; CYCLOMETHICONE 5; PEG-10 DIMETHICONE (600 CST); DIMETHICONOL (2000 CST); LAURYL PEG/PPG-18/18 METHICONE; CARBOMER HOMOPOLYMER, UNSPECIFIED TYPE; CAPRYLYL GLYCOL; SILANETRIOL; GLYCERIN; ISOHEXADECANE; UNDARIA PINNATIFIDA; SACCHAROMYCES CEREVISIAE; BUTYLENE GLYCOL; CAFFEINE; ISODODECANE; PALMITOYL TRIPEPTIDE-1; WATER; PALMITOYL TETRAPEPTIDE-7; SAMBUCUS NIGRA FLOWER

ACTIVE INGREDIENT: Zinc Oxide 9%

PURPOSE:Sunscreen

INDICATIONS AND USAGE

DIRECTIONS: • Apply liberally 15 minutes before sun exposure
• Use a water resistant product if swimming or sweating.
• Reapply at least every 2 hours • Children under 6 months:
Ask a doctor • Sun Protection Measures: Spending time in
the sun increases your risk of skin cancer and early skin aging.
To decrease this risk, regularly use a sunscreen with a broad
spectrum SPF value of 15 or higher and other sun protection
measures including: • Limit time in the sun, especially from
10 am - 2 pm • Wear long-sleeved shirts, pants, hats,
and sunglasses

INACTIVE INGREDIENTS: Butylene Glycol, Caffeine,
Carbomer, Caprylhydroxamic Acid, Caprylyl Glycol, Corallina
Officinalis Extract, Cyclohexasiloxane, Cyclopentasiloxane,
Dimethicone Crosspolymer, Dimethicone/Vinyl Dimethicone
Crosspolymer, Dimethiconol, Glycerin, Hydrogen
Dimethicone, Isododecane, Isohexadecane, Lauryl
PEG/PPG-18/18 Methicone, Palmitoyl Tripeptide-1, Palmitoyl
Tetrapeptide-7, PEG-10 Dimethicone, Polysorbate 20,
Saccharomyces/Selenium Ferment, Sambucus Nigra Flower
Extract, Siloxanetriol Alginate, Tetrahexyldecyl Ascorbate,
Tocopheryl Acetate, Undaria Pinnatifida Extract, Water

OTHER INFORMATION: • Protect this product from excessive
heat and direct sun

WARNINGS

WARNINGS: For external use only. Do not use on damaged
or broken skin. Stop use and ask a doctor if rash occurs. When
using this product, keep out of eyes. Rinse with water to
remove. Keep out of reach of children. If swallowed, get
medical help or contact a Poison Control Center right away.

Keep out of the reach of
children.

DOSAGE AND ADMINISTRATION

Helps prevent sunburn. If used as directed with other sun
protection measures (see Directions), decreases the risk of skin
cancer and early skin aging caused by the sun.

Apply liberally 15 minutes before sun exposure.

Principal Display Panel – 15 g Bottle Label

Proceuticals

PRIVATE LABEL by TiZO

eye repair non-tinted
mineral sunscreen

broad spectrum spf 20 with
gentle zinc oxide, peptides
& botanical blend

net wt. 0.5 oz. / 15 g

Graphic-Untitled